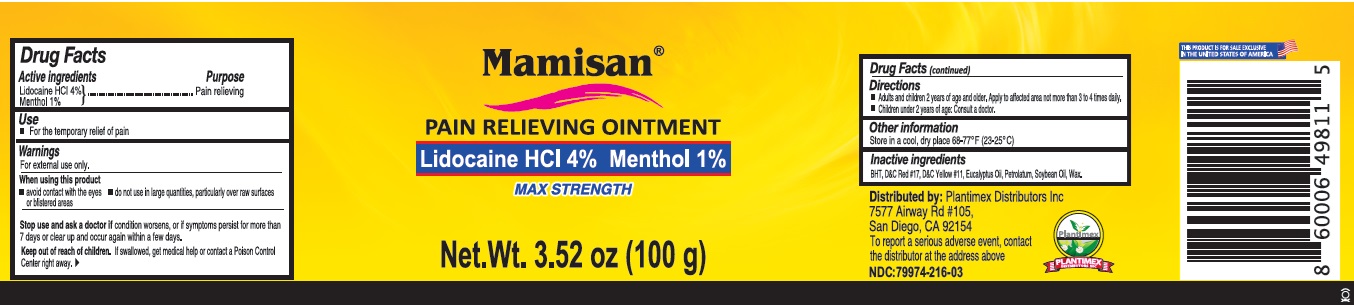 DRUG LABEL: Mamisan
NDC: 79974-216 | Form: OINTMENT
Manufacturer: Miramar Cosmetics, Inc DBA Miramar Lab
Category: otc | Type: HUMAN OTC DRUG LABEL
Date: 20260112

ACTIVE INGREDIENTS: LIDOCAINE HYDROCHLORIDE 4 g/100 g; MENTHOL, UNSPECIFIED FORM 1 g/100 g
INACTIVE INGREDIENTS: BUTYLATED HYDROXYTOLUENE; D&C RED NO. 17; D&C YELLOW NO. 11; EUCALYPTUS OIL; WHITE PETROLATUM; SOYBEAN OIL; GLYCERYL MONOSTEARATE

Mamisan®

Active ingredients

Lidocaine HCl 4%

Menthol 1%

Purpose

Pain relieving

Use

• For the temporary relief of pain

Warnings

For external use only.

When using this product

• avoid contact with the eyes • do not use in large quantities, particularly over raw surfaces or blistered areas

Stop use and ask a doctor if condition worsens, or if symptoms persist for more than 7 days or clear up and occur again within a few days.

Keep out of reach of children. If swallowed, get medical help or contact a Poison Control Center right away.

Directions

• Adults and children 2 years of age and older. Apply to affected area not more than 3 to 4 times daily.

• Children under 2 years of age: Consult a doctor.

Other information

Store in a cool, dry place 68-77°F (23-25°C)

Inactive ingredients

BHT, D&C Red #17, D&C Yellow #11, Eucalyptus Oil, Petrolatum, Soybean Oil, Wax.

MAX STRENGTH

Distributed by: Plantimex Distributors Inc
7577 Airway Rd #105,
San Diego, CA 92154
To report a serious adverse event, contact the distributor at the address above